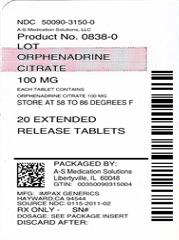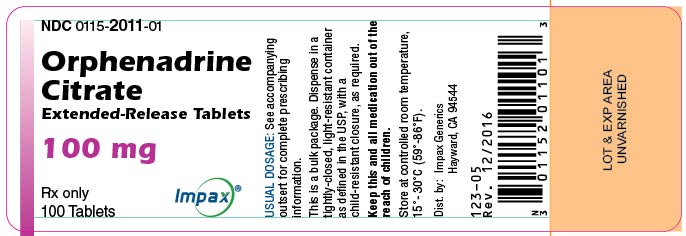 DRUG LABEL: Orphenadrine Citrate
NDC: 50090-3150 | Form: TABLET, EXTENDED RELEASE
Manufacturer: A-S Medication Solutions
Category: prescription | Type: HUMAN PRESCRIPTION DRUG LABEL
Date: 20190426

ACTIVE INGREDIENTS: ORPHENADRINE CITRATE 100 mg/1 1
INACTIVE INGREDIENTS: ETHYLCELLULOSE, UNSPECIFIED; POVIDONE, UNSPECIFIED; LACTOSE MONOHYDRATE; MAGNESIUM STEARATE

Orphenadrine Citrate
Extended-release Tablets, 100 mg

Rx only

DESCRIPTION

Orphenadrine citrate is the citrate salt of orphenadrine (2-dimethylaminoethyl 2-methylbenzhydryl ether citrate). It occurs as a white, crystalline powder having a bitter taste. It is practically odorless; sparingly soluble in water, slightly soluble in alcohol. Each orphenadrine citrate tablet contains 100 mg orphenadrine citrate, USP. Orphenadrine citrate tablets also contain ethylcellulose NF, povidone USP, lactose monohydrate NF, and magnesium stearate NF.

ACTIONS

The mode of therapeutic action has not been clearly identified, but may be related to its analgesic properties. Orphenadrine citrate also possesses anticholinergic actions.

INDICATIONS

Orphenadrine citrate is indicated as an adjunct to rest, physical therapy, and other measures for the relief of discomfort associated with acute painful musculo-skeletal conditions. The mode of action of the drug has not been clearly identified, but may be related to its analgesic properties. Orphenadrine citrate does not directly relax tense skeletal muscles in man.

CONTRAINDICATIONS

Contraindicated in patients with glaucoma, pyloric or duodenal obstruction, stenosing peptic ulcers, prostatic hypertrophy or obstruction of the bladder neck, cardiospasm (megaesophagus) and myasthenia gravis. Contraindicated in patients who have demonstrated a previous hypersensitivity to the drug.

WARNINGS

Some patients may experience transient episodes of light-headedness, dizziness or syncope. Orphenadrine citrate may impair the ability of the patient to engage in potentially hazardous activities such as operating machinery or driving a motor vehicle; ambulatory patients should therefore be cautioned accordingly.

PREGNANCY

Pregnancy category C

Safe use of orphenadrine citrate has not been established with respect to adverse effects upon fetal development. Therefore, orphenadrine citrate should be used in women of childbearing potential and particularly during early pregnancy only when in the judgement of the physician the potential benefits outweigh the possible hazards.

USAGE IN CHILDREN

Safety and effectiveness in children have not been established; therefore, this drug is not recommended for use in the pediatric age group.

PRECAUTIONS

Confusion, anxiety and tremors have been reported in a few patients receiving propoxyphene and orphenadrine concomitantly. As these symptoms may be simply due to an additive effect, reduction of dosage and/or discontinuation of one or both agents is recommended in such cases. Orphenadrine citrate should be used with caution in patients with tachycardia, cardiac decompensation, coronary insufficiency, or cardiac arrhythmias. Safety of continuous long-term therapy with orphenadrine has not been established. Therefore, if orphenadrine is prescribed for prolonged use, periodic monitoring of blood, urine and liver function values is recommended.

ADVERSE REACTIONS

Adverse reactions of orphenadrine are mainly due to the mild anticholinergic action of orphenadrine, and are usually associated with higher dosage. Dryness of the mouth is usually the first adverse effect to appear. When the daily dose is increased, possible adverse effects include: tachycardia, palpitation, urinary hesitancy or retention, blurred vision, dilation of pupils, increased ocular tension, weakness, nausea, vomiting, headache, dizziness, constipation, drowsiness, hypersensitivity reactions, pruritus, hallucinations, agitation, tremor, gastric irritation, and rarely urticaria and other dermatoses. Infrequently, an elderly patient may experience some degree of mental confusion. These adverse reactions can usually be eliminated by reduction in dosage. Very rare cases of aplastic anemia associated with the use of orphenadrine tablets have been reported. No causal relationship has been established.

DOSAGE AND ADMINISTRATION

TABLETS

Adults-Two tablets per day; one in the morning and one in the evening.

HOW SUPPLIED

Product: 50090-3150

NDC: 50090-3150-0 20 TABLET, EXTENDED RELEASE in a BOTTLE

NDC: 50090-3150-1 30 TABLET, EXTENDED RELEASE in a BOTTLE, PLASTIC

NDC: 50090-3150-5 60 TABLET, EXTENDED RELEASE in a BOTTLE, PLASTIC

NDC: 50090-3150-2 14 TABLET, EXTENDED RELEASE in a BOTTLE, PLASTIC

Dist. by:
Impax Generics
Hayward, CA 94544

Rev. 10/2015
124-04

PRINCIPAL DISPLAY PANEL - 100 mg Tablet Bottle Label

Impax Generics

NDC 0115-2011-01

Orphenadrine
Citrate
Extended-Release Tablets

100 mg

Rx only

100 TABLETS

Storage

Store at controlled room temperature 15° to 30°C (59° to 86°F). Dispense in tightly-closed, light-resistant container (USP). Dist. by: Impax Generics Hayward, CA 94544